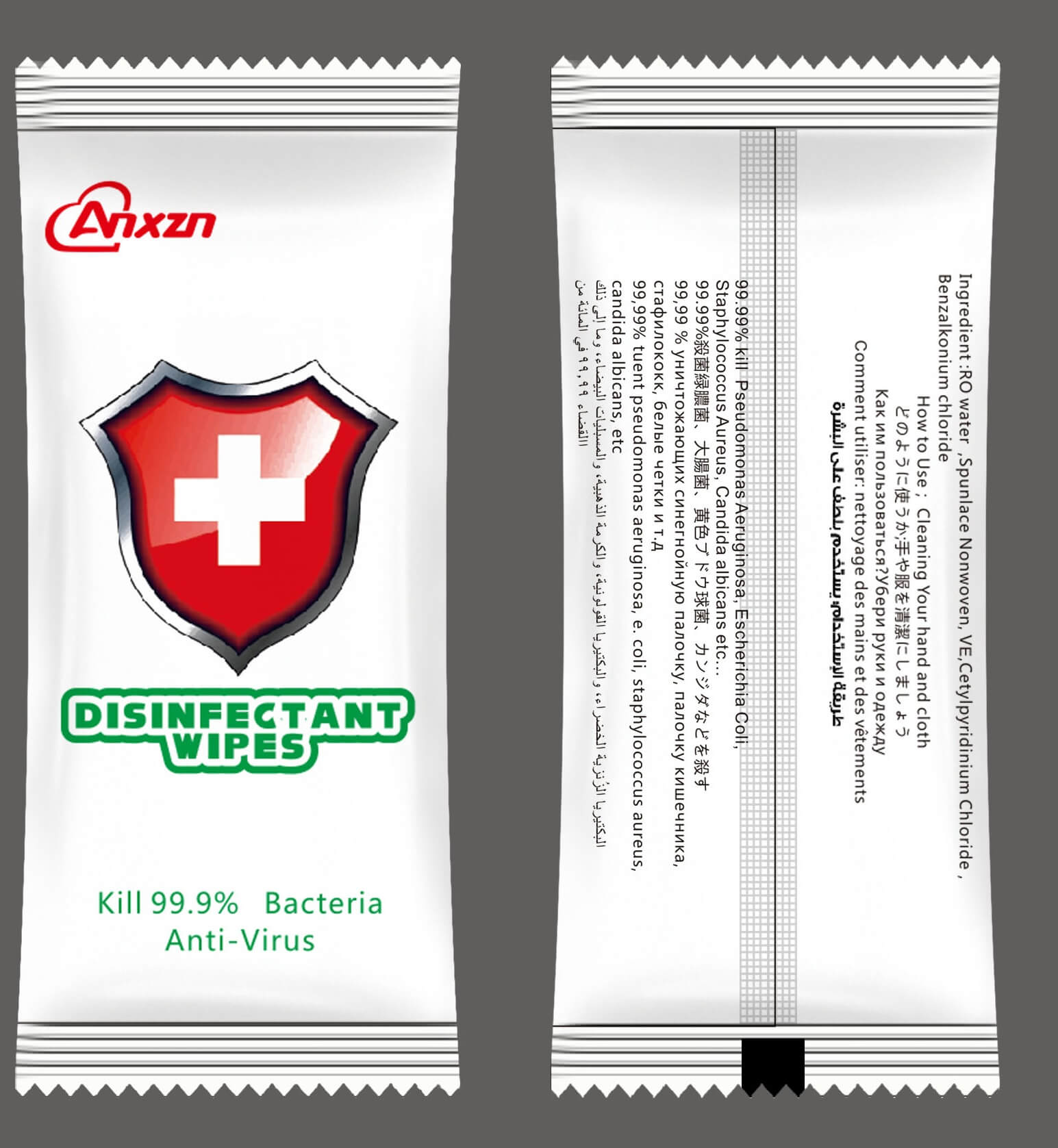 DRUG LABEL: Disinfectant Wipes
NDC: 76641-001 | Form: CLOTH
Manufacturer: FuYang YangYang Health Technology Co. Ltd
Category: otc | Type: HUMAN OTC DRUG LABEL
Date: 20200702

ACTIVE INGREDIENTS: BENZALKONIUM CHLORIDE 2 mg/100 1; CETYLPYRIDINIUM CHLORIDE 1 mg/100 1
INACTIVE INGREDIENTS: PROPYLENE GLYCOL; GLYCERIN; TOCOPHEROL; WATER

74641-001

Active Ingredient(s)

BENZALKONIUM CHLORIDE,CETYLPYRIDINIUM CHLORIDE

Purpose

Antibacterial

Use

Open the cover whenusing, tear of the adhesive tape, can be exracteduse. use Afer, please fimely reduce the adhesive paste and close the cover to avoid inemal moisure eaporation.

Warnings

1. This product is only for daily use and should be stored in a cool and sealed place.
2. For extemal use only. If you find any skin discomfort or sensitivity, please stop using immediately.
3. wipe the entryable items to be used after vlatilization;
4. This product cannot be dissolved. Please do not throw it into the toilt.
5. Iflammables, do not go near the source of fire.

Do not use

- in children less than 2 months of age
- on open skin wounds

When using this product keep out of eyes, ears, and mouth. In case of contact with eyes, rinse eyes thoroughly with water.
Stop use and ask a doctor if irritation or rash occurs. These may be signs of a serious condition.
Keep out of reach of children. If swallowed, get medical help or contact a Poison Control Center right away.

Stop use and ask a doctor if irritation or rash occurs. These may be signs of a serious condition.

Keep out of reach of children. If swallowed, get medical help or contact a Poison Control Center right away.

Directions

- Place enough product on hands to cover all surfaces. Rub hands together until dry.
- Supervise children under 6 years of age when using this product to avoid swallowing.

Other information

- Store between 15-30C (59-86F)
- Avoid freezing and excessive heat above 40C (104F)

Inactive ingredients

purified water USP,GLYCERIN,GLYCERIN,GLYCERIN

Package Label - Principal Display Panel

1 CLOTH in 1 BAG NDC: 76641-001-01

10 CLOTH in 1 BAG NDC: 76641-001-02

50 CLOTH in 1 BAG NDC: 76641-001-03

100 CLOTH in 1 BAG NDC: 76641-001-01